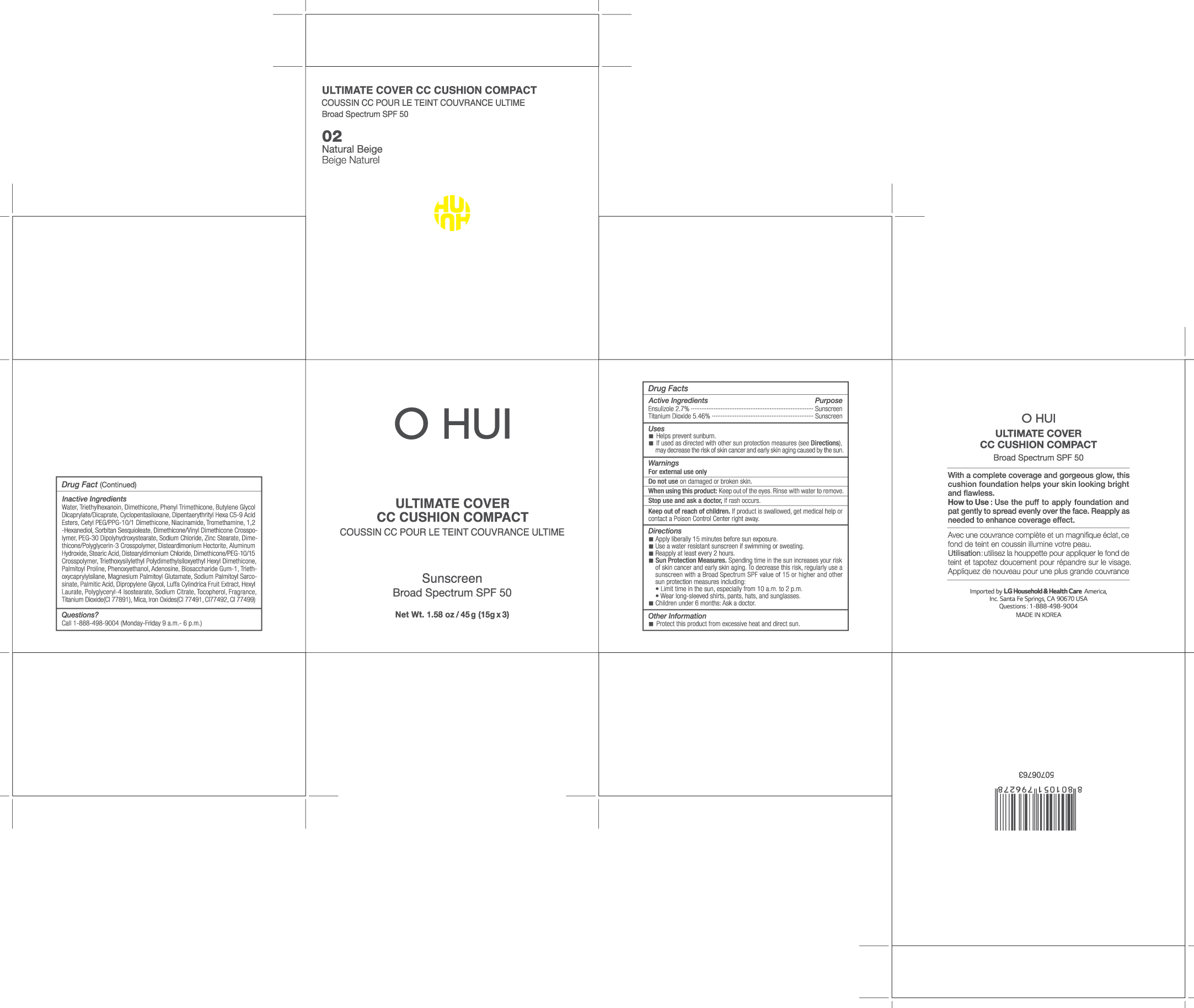 DRUG LABEL: OHUI Ultimate Cover CC Cushion Compact 02 Natural Beige
NDC: 53208-601 | Form: POWDER
Manufacturer: LG H&H Co., Ltd.
Category: otc | Type: HUMAN OTC DRUG LABEL
Date: 20250101

ACTIVE INGREDIENTS: TITANIUM DIOXIDE 0.819 g/15 g; ENSULIZOLE 0.405 g/15 g
INACTIVE INGREDIENTS: DIMETHICONE; ZINC STEARATE; TRIETHYLHEXANOIN; DISTEARDIMONIUM HECTORITE; PALMITIC ACID; NIACINAMIDE; TROMETHAMINE; SORBITAN SESQUIOLEATE; DIMETHICONE/VINYL DIMETHICONE CROSSPOLYMER (SOFT PARTICLE); SODIUM CHLORIDE; PALMITOYL PROLINE; POLYGLYCERYL-4 ISOSTEARATE; WATER; PHENYL TRIMETHICONE; BUTYLENE GLYCOL DICAPRYLATE/DICAPRATE; CETYL PEG/PPG-10/1 DIMETHICONE (HLB 2); 1,2-HEXANEDIOL; STEARIC ACID; CYCLOMETHICONE 5; DIPENTAERYTHRITYL HEXA C5-9 ACID ESTERS; PEG-30 DIPOLYHYDROXYSTEARATE; ALUMINUM HYDROXIDE; DISTEARYLDIMONIUM CHLORIDE; PHENOXYETHANOL; ADENOSINE; BIOSACCHARIDE GUM-1; TRIETHOXYCAPRYLYLSILANE; MAGNESIUM PALMITOYL GLUTAMATE; SODIUM PALMITOYL SARCOSINATE; DIPROPYLENE GLYCOL; LUFFA AEGYPTIACA FRUIT; HEXYL LAURATE; SODIUM CITRATE; TOCOPHEROL; MICA

53208-601-03 OHUI Ultimate Cover CC Cushion Compact 02 Natural Beige

ACTIVE INGREDIENTS

ENSULIZOLE 2.7%, TITANIUM DIOXIDE 5.46%

Purpose

Sunscreen

Uses

Helps prevent sunburn. If used as directed with other sun protection measures (see Directions), decreases the risk of skin cancer and early skin aging caused by the sun exposure.

Warnings

For external use only. Do not use on damaged or broken skin. When using this product: Keep out of the eyes. Rinse with water to remove. Stop use and ask a doctor, if rash occurs. Keep out of reach of children. If product is swallowed, get medical help or contact a Poison Control Center right away.

Keep out of reach of children. If product is swallowed, get medical help or contact a Poison Control Center right away.

Directions

Apply liberally 15 minutes before sun exposure. Use a water resistant sunscreen if swimming or sweating. Reapply at least every 2 hours. Sun Protection Measures. Spending time in the sun increases your risk of skin cancer and early skin aging. To decrease this risk, regulary use a sunscreen with a Broad Spectrum SPF value of 15 or higher and other sun protection measures including: Limit time in the sun, especially from 10 a.m. to 2 p.m. Wear long-sleeved shirts, pants, hats, and sunglasses. Children under 6 months: Ask a doctor.

Other Information

Protect this product from excessive heat and direct sun.

Inactive Ingredients

Water

INACTIVE INGREDIENTS

WATER, TRIETHYLHEXANOIN, DIMETHICONE, PHENYL TRIMETHICONE, BUTYLENE GLYCOL DICAPRYLATE/DICAPRATE, CYCLOPENTASILOXANE, DIPENTAERYTHRITYL HEXA C5-9 ACID ESTERS, CETYL PEG/PPG-10/1 DIMETHICONE, NIACINAMIDE, TROMETHAMINE, 1,2-HEXANEDIOL, SORBITAN SESQUIOLEATE, DIMETHICONE/VINYL DIMETHICONE CROSSPOLYMER, SODIUM CHLORIDE, ZINC STEARATE, PEG-30 DIPOLYHYDROXYSTEARATE, DIMETHICONE/POLYGLYCERIN-3 CROSSPOLYMER, DISTEARDIMONIUM HECTORITE, ALUMINUM HYDROXIDE, STEARIC ACID, DISTEARYLDIMONIUM CHLORIDE, DIMETHICONE/PEG-10/15 CROSSPOLYMER, TRIETHOXYSILYLETHYL POLYDIMETHYLSILOXYETHYL HEXYL DIMETHICONE, PALMITOYL PROLINE, PHENOXY ETHANOL, ADENOSINE, BIOSACCHARIDE GUM-1, TRIETHOXYCAPRYLYLSILANE, MAGNESIUM PALMITOYL GLUTAMATE, SODIUM PALMITOYL SARCOSINATE, PALMITIC ACID, DIPROPYLENE GLYCOL, LUFFA CYLINDRICA FRUIT EXTRACT, HEXYL LAURATE, SODIUM CITRATE, POLYGLYCERYL-4 ISOSTEARATE, TOCOPHEROL, FRAGRANCE, TITANIUM DIOXIDE(CI 77891), MICA, IRON OXIDES(CI 77492), IRON OXIDES(CI 77491), IRON OXIDES(CI 77499)

PRINCIPAL DISPLAY PANEL

O HUI

ULTIMATE COVER

CC CUSHION COMPACT
Sunscreen

Broad Spectrum SPF 50
Net Wt. 1.58 oz / 45 g (15 g x 3)